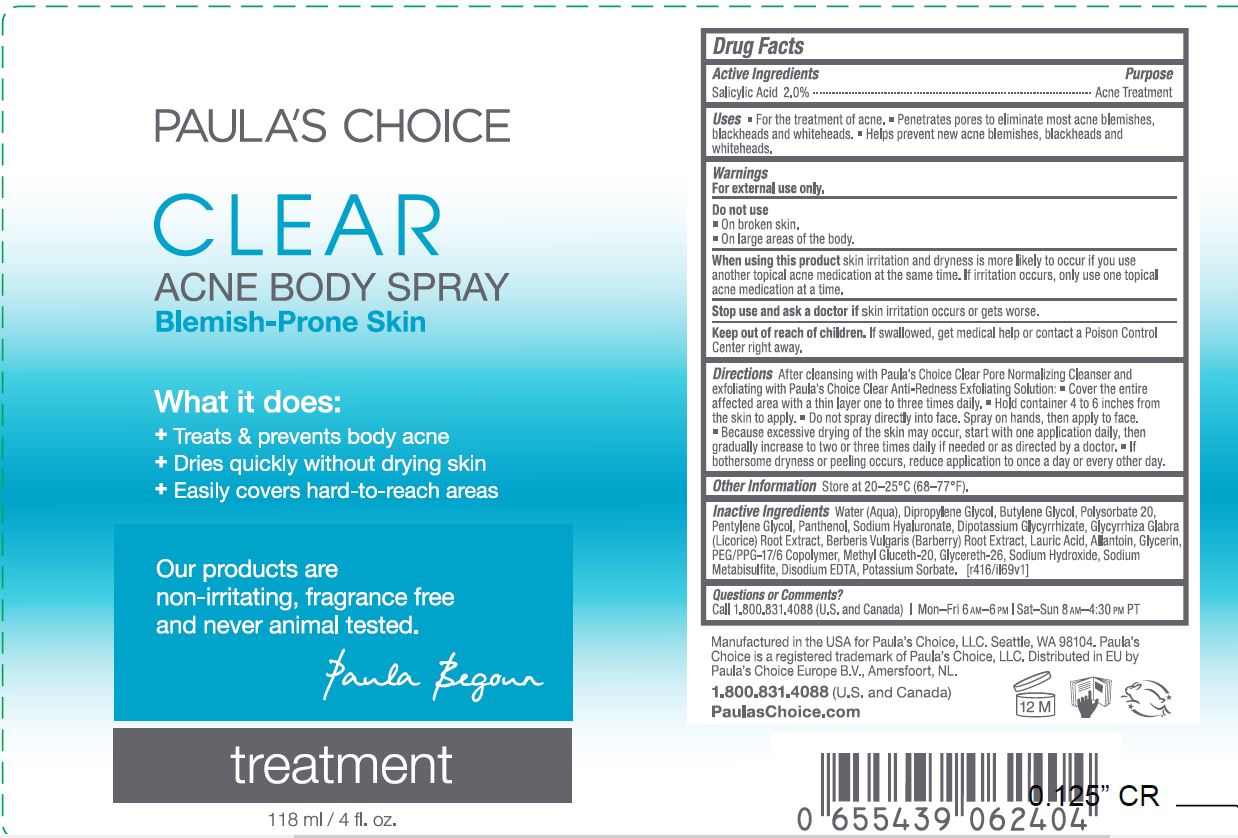 DRUG LABEL: Clear Acne Body
NDC: 56152-5000 | Form: SPRAY
Manufacturer: Cosmetic Enterprises Ltd
Category: otc | Type: HUMAN OTC DRUG LABEL
Date: 20251010

ACTIVE INGREDIENTS: SALICYLIC ACID 2 g/118 mL
INACTIVE INGREDIENTS: SODIUM METABISULFITE; EDETATE DISODIUM; POTASSIUM SORBATE; BUTYLENE GLYCOL; WATER; DIPROPYLENE GLYCOL; POLYSORBATE 20; PENTYLENE GLYCOL; PANTHENOL; HYALURONATE SODIUM; GLYCYRRHIZINATE DIPOTASSIUM; GLYCYRRHIZA GLABRA; BERBERIS VULGARIS ROOT; LAURIC ACID; ALLANTOIN; GLYCERIN; PEG/PPG-17/6 COPOLYMER; METHYL GLUCETH-20; GLYCERETH-26; SODIUM HYDROXIDE

Clear Acne Body Spray

Active Ingredients Purpose

Salicylic Acid 2.0% Acne Treatment

Uses

For the treatment of of Acne

Penetrates pores to eliminate most acne blemishes, blackheads, and whiteheads

Keep out of reach of children.If swallowed, get medical help or contact a Poison Crontrol Center right away.

Stop use and ask a doctor ifskin irritation occurs or gets worse.

Warnings

For external use only.

Do not use

on broken skin

on large areas of the body

When using this productskin irritation and dryness is mroe likely to occur if you use another topical acne medication at the same time. If irritation, only use one topical acne medication at a time

Directions

After cleansing with Paula's Choice Clear Pore Normalizing Cleanser and exfoliating with Paula's Choice Clear Anti-Redness Exfoliating Solution.

Cover the entire affected area with a thin layer one to three times daily.

Hold container 4 to 6 inches from the skin to apply.

Do not spray directly into face. Spray on hands, then apply to face.

Because excessive drying of the skin may occur, start with one application daily, then gradually increase to two or three times daily if needed or as directed by a doctor.

If bothersome dryness or peeling occurs, reduce application to once a day or every other day.

INACTIVE INGREDIENT

Inactive ingredientsWater (Aqua), Dipropylene Glycol, Butylene Glycol, Polysorbate 20, Pentylene Glycol, Panthenol, Sodium Hyaluronate, Dipotassium Glycyrrhizate, Glycyrrhiza Glabra (Licorice) Root Extract, Berberis Vulgaris (Barberry) Root Extract, Lauric Acid, Allantoin, Glycerin, PEG/PPG-17/6 Copolymer, Methyl Gluceth-20, Glycereth-26, Sodium Hydroxide, Sodium Metabisulfite, Disodium EDTA, Potassium Sorbate

PACKAGE LABEL

Paula's Choice

Clear Acne Body Spray

118ml/ 4 fl oz